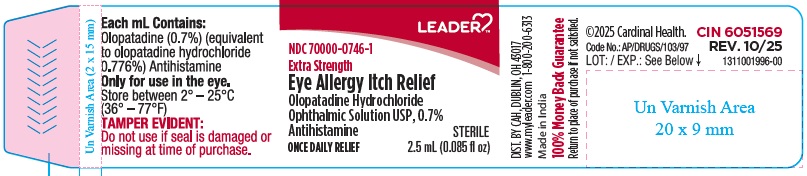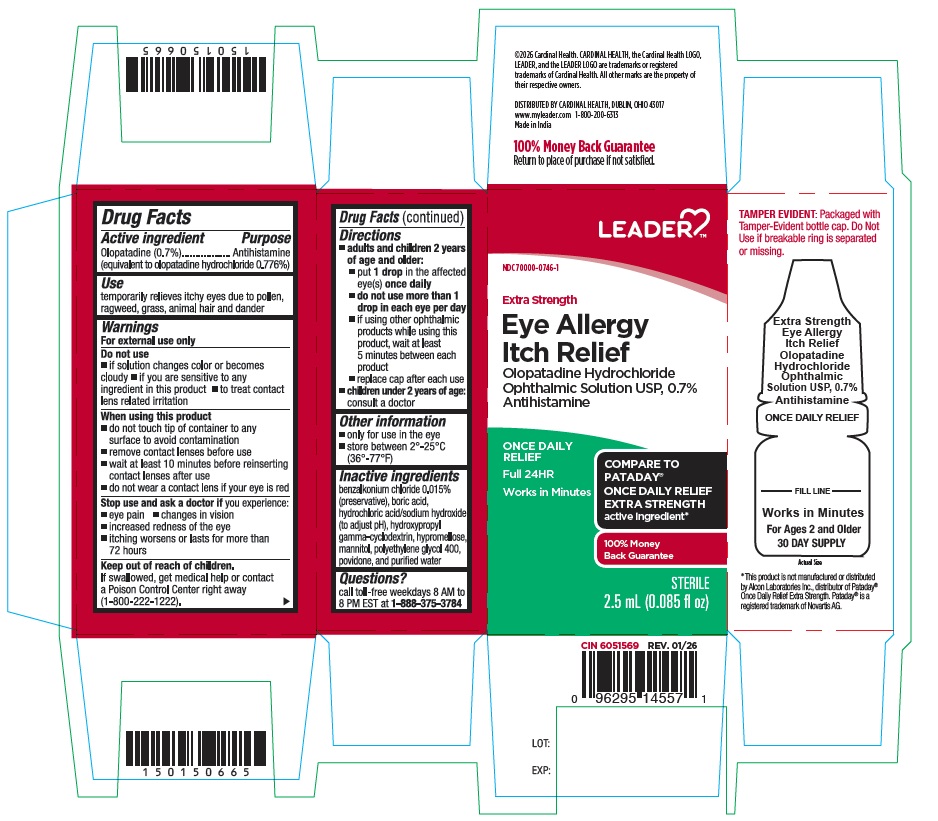 DRUG LABEL: Eye Allergy Itch Relief
NDC: 70000-0746 | Form: SOLUTION/ DROPS
Manufacturer: CARDINAL HEALTH 110, LLC. DBA LEADER
Category: otc | Type: Human OTC Drug Label
Date: 20260224

ACTIVE INGREDIENTS: OLOPATADINE HYDROCHLORIDE 7 mg/1 mL
INACTIVE INGREDIENTS: BENZALKONIUM CHLORIDE; BORIC ACID; HYDROCHLORIC ACID; HYDROXYPROPYL .GAMMA.-CYCLODEXTRIN; HYPROMELLOSE 2910 (4000 MPA.S); MANNITOL; POLYETHYLENE GLYCOL 400; POVIDONE K30; SODIUM HYDROXIDE; WATER

ACTIVE INGREDIENT

Olopatadine (0.7%) (equivalent to olopatadine hydrochloride 0.776%)

PURPOSE

Antihistamine

USE

temporarily relieves itchy eyes due to pollen, ragweed, grass, animal hair and dander

WARNINGS

For external use only

DO NOT USE

• if solution changes color or becomes cloudy
• if you are sensitive to any ingredient in this product
• to treat contact lens related irritation

WHEN USING THIS PRODUCT

• do not touch tip of container to any surface to avoid contamination
• remove contact lenses before use
• wait at least 10 minutes before reinserting contact lenses after use
• do not wear a contact lens if your eye is red

STOP USE AND ASK DOCTOR IF

you experience:

- eye pain
- changes in vision
- increased redness of the eye
- itching worsens or lasts for more than 72 hours

KEEP OUT OF REACH OF CHILDREN

If swallowed, get medical help or contact a Poison Control Center right away(1-800-222-1222).

DIRECTIONS

- adults and children 2 years of age and older:
- put 1 drop in the affected eye(s) once daily
- do not use more than 1 drop in each eye per day
- if using other ophthalmic products while using this product, wait at least 5 minutes between each product
- replace cap after each use
- children under 2 years of age: consult a doctor

OTHER INFORMATION

• only for use in the eye
• store between 2° to 25°C (36° to 77°F)

INACTIVE INGREDIENTS

benzalkonium chloride 0.015% (preservative), boric acid, hydrochloric acid/sodium hydroxide (to adjust pH), hydroxypropyl gamma-cyclodextrin, hypromellose, mannitol, polyethylene glycol 400, povidone and purified water.

QUESTIONS?

call toll-free weekdays 8 AM to 8 PM EST at 1-888-375-3784

Distributed by:

CARDINAL HEALTH,

DUBLIN, OHIO 43017

www.myleader.com

1-800-200-6313

Made in India

©2025 Cardinal Health. CARDINAL HEALTH, the Cardinal Health LOGO, LEADER, and the LEADER LOGO are trademarks or registered trademarks of Cardinal Health. All other marks are the property of their respective owners.

100% Money Back Guarantee

Return to place of purchase if not satisfied.

CIN 6051569

Rev . 01/26

*This product is not manufactured or distributed by Alcon Laboratories Inc., distributor of Pataday® Once Daily Relief Extra Strength. Pataday® is a registered trademark of Novartis AG.

PRINCIPAL DISPLAY PANEL

Carton Label:

NDC 70000-0746-1

Extra Strength

Eye Allergy Itch Relief

Olopatadine Hydrochloride
Ophthalmic Solution USP, 0.7%
Antihistamine

ONCE DAILY RELIEF

Full 24HR

Works in Minutes

Sterile

2.5 mL (0.085 fl oz)

Compare to Pataday Once Daily Relief Extra Strength active ingredient*

TAMPER EVIDENT: Packaged with Tamper-Evident bottle cap. Do Not Use if breakable ring is separated or missing.

For Ages 2 and Older

30 DAY SUPPLY

Bottle Label:
Extra Strength

Eye Allergy Itch Relief

Olopatadine Hydrochloride
Ophthalmic Solution USP, 0.7%
Antihistamine
ONCE DAILY RELIEF

Sterile
2.5 mL (0.085 fl oz)